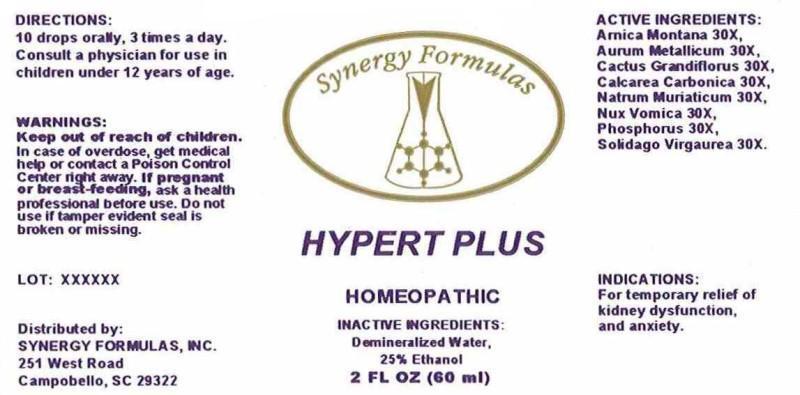 DRUG LABEL: HYPERT PLUS
NDC: 43772-0042 | Form: LIQUID
Manufacturer: Synergy Formulas, Inc.
Category: homeopathic | Type: HUMAN OTC DRUG LABEL
Date: 20140925

ACTIVE INGREDIENTS: ARNICA MONTANA 30 [hp_X]/1 mL; GOLD 30 [hp_X]/1 mL; SELENICEREUS GRANDIFLORUS STEM 30 [hp_X]/1 mL; OYSTER SHELL CALCIUM CARBONATE, CRUDE 30 [hp_X]/1 mL; SODIUM CHLORIDE 30 [hp_X]/1 mL; STRYCHNOS NUX-VOMICA SEED 30 [hp_X]/1 mL; PHOSPHORUS 30 [hp_X]/1 mL; SOLIDAGO VIRGAUREA FLOWERING TOP 30 [hp_X]/1 mL
INACTIVE INGREDIENTS: WATER; ALCOHOL

DRUG FACTS

ACTIVE INGREDIENTS:

ARNICA MONTANA 30X, AURUM METALLICUM 30X, CACTUS GRANDIFLORUS 30X, CALCAREA CARBONICA 30X, NATRUM MURIATICUM 30X, NUX VOMICA 30X, PHOSPHORUS 30X, SOLIDAGO VIRGAUREA 30X.

INDICATIONS:

For temporary relief of kidney dysfunction, and anxiety.

WARNINGS:

Keep out of reach of children. In case of overdose, get medical help or contact a Poison Control Center right away.

If pregnant or breast-feeding, ask a health professional before use.

Do not use if tamper evident seal is broken or missing.

Keep out of reach of children. In case of overdose, get medical help or contact a Poison Control Center right away.

DIRECTIONS:

10 drops orally, 3 times a day.

Consult a physician for use in children under 12 years of age.

INDICATIONS:

For temporary relief of kidney dysfunction, and anxiety.

INACTIVE INGREDIENTS:

Demineralized Water, 25% Ethanol.

QUESTIONS:

Distributed by:

SYNERGY FORMULAS, INC.

251 West Road

Campobello, SC 29332

PACKAGE LABEL DISPLAY:

Synergy Formulas

HYPERT PLUS

HOMEOPATHIC

2 FL OZ (60 ml)